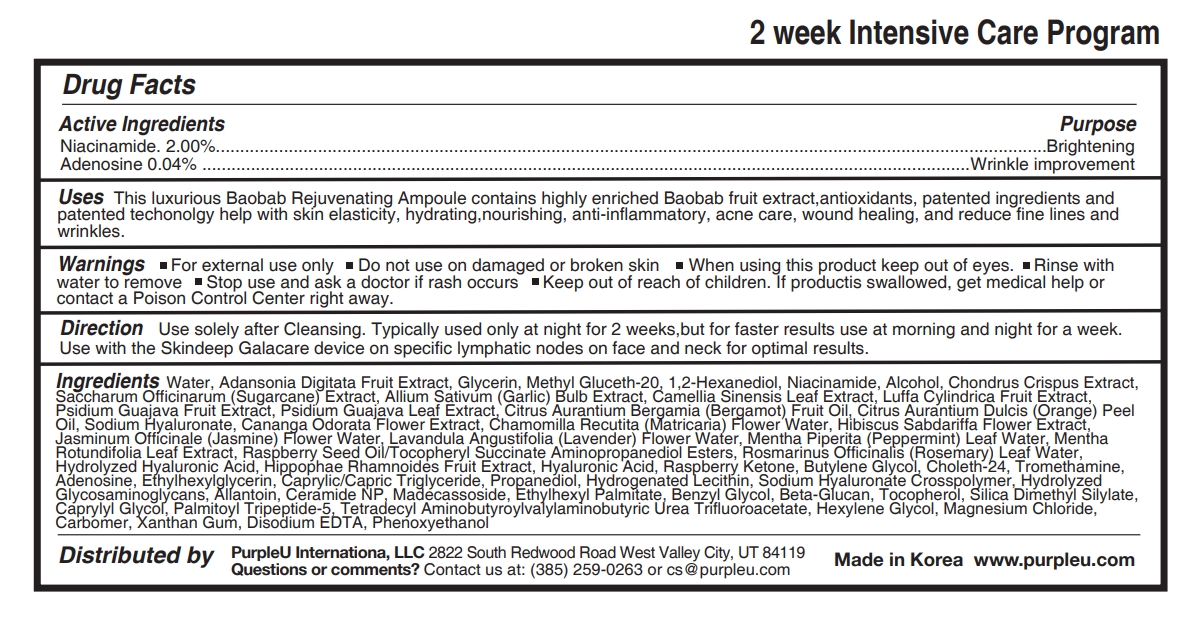 DRUG LABEL: PurpleU BAOBAB REJUVENATING AMPOULE
NDC: 90069-205 | Form: LIQUID
Manufacturer: Purple U Co., Ltd
Category: otc | Type: HUMAN OTC DRUG LABEL
Date: 20200902

ACTIVE INGREDIENTS: ADENOSINE 0.04 g/100 mL; NIACINAMIDE 2 g/100 mL
INACTIVE INGREDIENTS: GARLIC; PSIDIUM GUAJAVA LEAF; HYALURONATE SODIUM; CANANGA ODORATA FLOWER; CHAMOMILE FLOWER OIL; HIBISCUS SABDARIFFA FLOWER; JASMINUM OFFICINALE FLOWER; LAVENDER OIL; PEPPERMINT OIL; MENTHA X ROTUNDIFOLIA LEAF; HIPPOPHAE RHAMNOIDES FRUIT; 4-(P-HYDROXYPHENYL)-2-BUTANONE; BUTYLENE GLYCOL; CHOLETH-24; TROMETHAMINE; ETHYLHEXYLGLYCERIN; TOCOPHEROL; SILICA DIMETHYL SILYLATE; CAPRYLYL GLYCOL; PALMITOYL TRIPEPTIDE-5; HEXYLENE GLYCOL; CARBOMER HOMOPOLYMER, UNSPECIFIED TYPE; XANTHAN GUM; PHENOXYETHANOL; ROSEMARY OIL; HYALURONIC ACID; MEDIUM-CHAIN TRIGLYCERIDES; PROPANEDIOL; HYDROGENATED SOYBEAN LECITHIN; HYDROLYZED GLYCOSAMINOGLYCANS (BOVINE; 50000 MW); ALLANTOIN; CERAMIDE 3; MADECASSOSIDE; ETHYLHEXYL PALMITATE; ETHYLENE GLYCOL MONOBENZYL ETHER; TETRADECYL AMINOBUTYROYLVALYLAMINOBUTYRIC UREA TRIFLUOROACETATE; MAGNESIUM CHLORIDE; EDETATE DISODIUM ANHYDROUS; GREEN TEA LEAF; LUFFA AEGYPTIACA FRUIT; GUAVA; BERGAMOT OIL; ORANGE OIL; WATER; ADANSONIA DIGITATA FRUIT; GLYCERIN; METHYL GLUCETH-20; 1,2-HEXANEDIOL; ALCOHOL; CHONDRUS CRISPUS CARRAGEENAN; SUGARCANE

90069-205

Active Ingredients

Niacinamide. 2.00%

Adenosine 0.04%

Purpose

Brightening

Wrinkle improvement

Uses

This luxurious Baobab Rejuvenating Ampoule contains highly enriched Baobab fruit extract,antioxidants, patented ingredients and patented techonolgy help with skin elasticity, hydrating,nourishing, anti-inflammatory, acne care, wound healing, and reduce fine lines and wrinkles.

Warnings

- For external use only
- Do not use on damaged or broken skin
- When using this product keep out of eyes.
- Rinse with water to remove

Stop use and ask a doctor if

rash occurs

Keep out of reach of children.

If productis swallowed, get medical help or contact a Poison Control Center right away.

Direction

Use solely after Cleansing. Typically used only at night for 2 weeks,but for faster results use at morning and night for a week. Use with the Skindeep Galacare device on specific lymphatic nodes on face and neck for optimal results.

Ingredients

Water, Adansonia Digitata Fruit Extract, Glycerin, Methyl Gluceth-20, 1,2-Hexanediol, Niacinamide, Alcohol, Chondrus Crispus Extract, Saccharum Officinarum (Sugarcane) Extract, Allium Sativum (Garlic) Bulb Extract, Camellia Sinensis Leaf Extract, Luffa Cylindrica Fruit Extract, Psidium Guajava Fruit Extract, Psidium Guajava Leaf Extract, Citrus Aurantium Bergamia (Bergamot) Fruit Oil, Citrus Aurantium Dulcis (Orange) Peel Oil, Sodium Hyaluronate, Cananga Odorata Flower Extract, Chamomilla Recutita (Matricaria) Flower Water, Hibiscus Sabdariffa Flower Extract, Jasminum Officinale (Jasmine) Flower Water, Lavandula Angustifolia (Lavender) Flower Water, Mentha Piperita (Peppermint) Leaf Water, Mentha Rotundifolia Leaf Extract, Raspberry Seed Oil/Tocopheryl Succinate Aminopropanediol Esters, Rosmarinus Officinalis (Rosemary) Leaf Water, Hydrolyzed Hyaluronic Acid, Hippophae Rhamnoides Fruit Extract, Hyaluronic Acid, Raspberry Ketone, Butylene Glycol, Choleth-24, Tromethamine, Adenosine, Ethylhexylglycerin, Caprylic/Capric Triglyceride, Propanediol, Hydrogenated Lecithin, Sodium Hyaluronate Crosspolymer, Hydrolyzed Glycosaminoglycans, Allantoin, Ceramide NP, Madecassoside, Ethylhexyl Palmitate, Benzyl Glycol, Beta-Glucan, Tocopherol, Silica Dimethyl Silylate, Caprylyl Glycol, Palmitoyl Tripeptide-5, Tetradecyl Aminobutyroylvalylaminobutyric Urea Trifluoroacetate, Hexylene Glycol, Magnesium Chloride, Carbomer, Xanthan Gum, Disodium EDTA, Phenoxyethanol